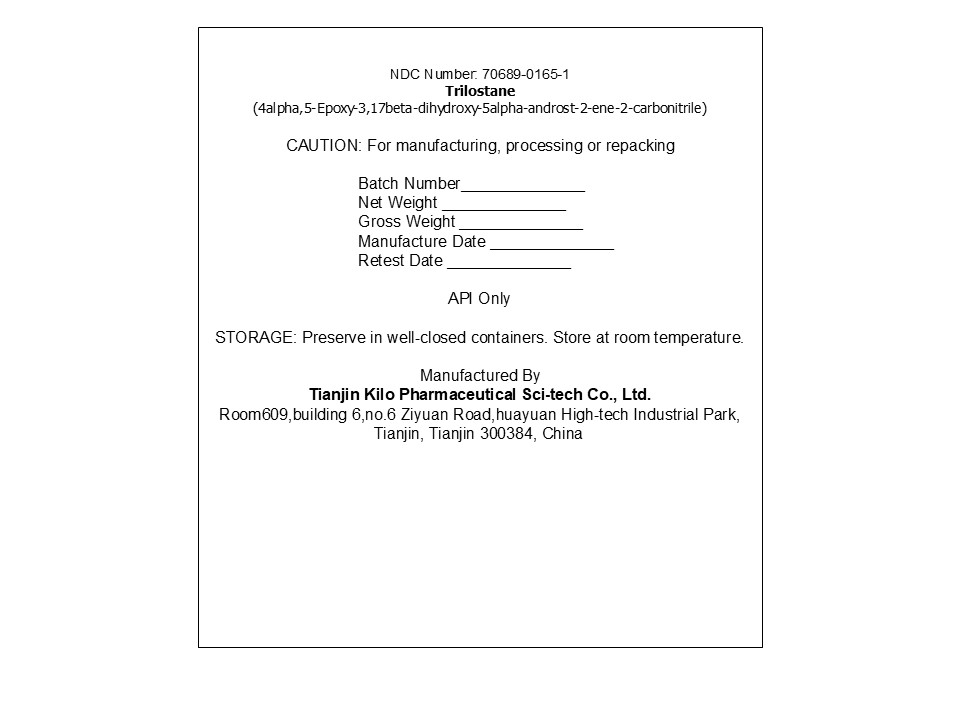 DRUG LABEL: Trilostane
NDC: 70689-0165 | Form: POWDER
Manufacturer: Tianjin Kilo Pharmaceutical Scitech Co Ltd
Category: other | Type: BULK INGREDIENT - ANIMAL DRUG
Date: 20251217

ACTIVE INGREDIENTS: Trilostane 1 kg/1 kg

PACKAGE LABEL

NDC Number: 70689-0165-1
Trilostane
(4alpha,5-Epoxy-3,17beta-dihydroxy-5alpha-androst-2-ene-2-carbonitrile)

CAUTION: For manufacturing, processing or repacking

Batch Number______________
Net Weight ______________
Gross Weight ______________
Manufacture Date ______________
Retest Date ______________

API Only

STORAGE: Preserve in well-closed containers. Store at room temperature.

Manufactured By
Tianjin Kilo Pharmaceutical Sci-tech Co., Ltd.
Room609,building 6,no.6 Ziyuan Road,huayuan High-tech Industrial Park, Tianjin, Tianjin 300384, China